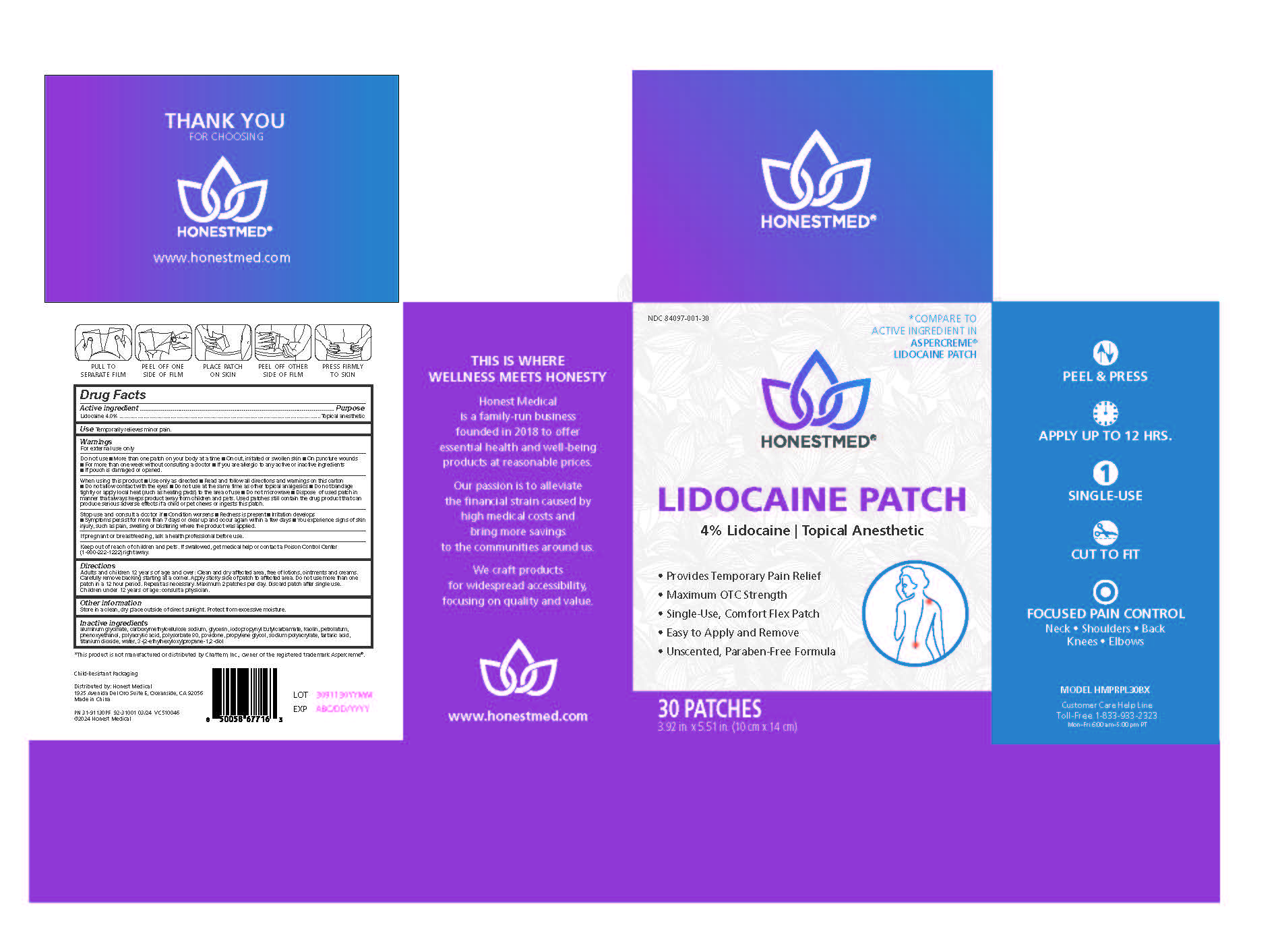 DRUG LABEL: Honest Med Lidocaine Pain Relief Patch
NDC: 84097-001 | Form: PATCH
Manufacturer: Proper Buys LLC
Category: otc | Type: HUMAN OTC DRUG LABEL
Date: 20251228

ACTIVE INGREDIENTS: LIDOCAINE 4 g/100 g
INACTIVE INGREDIENTS: ETHYLHEXYLGLYCERIN; PETROLATUM; PHENOXYETHANOL; DIHYDROXYALUMINUM AMINOACETATE; GLYCERIN; KAOLIN; POLYACRYLIC ACID (8000 MW); POLYSORBATE 80; PROPYLENE GLYCOL; IODOPROPYNYL BUTYLCARBAMATE; POVIDONE; SODIUM POLYACRYLATE (8000 MW); TARTARIC ACID; TITANIUM DIOXIDE; WATER; CARBOXYMETHYLCELLULOSE SODIUM, UNSPECIFIED FORM

Honest Med Lidocaine Pain Relief Patch 30-Count

Active Ingredients

Lidocaine 4% . . . . . . . . . . . . . . . . . . . . . . . . . . . . . . Topical Anesthetic

Purpose

Topical anesthetic

Dosage and Administration

Directions Adults and children over 12 years:

■ clean and dry affected area, free of lotions, ointments and creams.

■ carefully remove backing from patch starting at corner

■ apply sticky side of patch to affected area

■ Do not use more than one patch in a 12 hour period. Repeat as necessary. Maximum 2 patches per day. Discard patch after single use. Children under 12 years of age: consult a physician.

Warnings

For external use only.

Indications and Usage

Uses: Temporaily relieves minor pains.

When using this product

■ use only as directed

■ read and follow all directions and warnings on this carton

■ do not allow contact with the eyes

■ do not use at the same time as other topical analgesics

■ do not bandage tightly or apply local heat (such as heating pads) to the area of use

■ do not microwave

■ dispose of used patch in manner that always keeps product away from children and pets. Used patches still contain the drug product that can produce serious adverse effects if a child or pet chews or ingests this patch.

Stop use and consult a doctor

■ condition worsens

■ redness is present

■ irritation develops

■ symptoms persist for more than 7 days or clear up and occur again within a few days

■ you experience signs of skin injury, such as pain, swelling or blistering where the product was applied.

PREGNANCY OR BREAST FEEDING

If pregnant or breastfeeding, ask a health professional before use.

Do not Use

■ more than one patch on your body at a time

■ on cut, irritated or swollen skin

■ on puncture wounds

■ for more than one week without consulting a doctor

■ if you are allergic to any active or inactive ingredients

■ if pouch is damaged or opened.

Keep out of reach of children and pets.

If swallowed, get medical help or contact a Poison Control Center (1-800-222-1222) right away.

Other Safety Information

Store in a clean, dry place outside of direct sunlight. Protect from excessive moisture.

Inactive Ingredients

aluminum glycinate, carboxymethylcellulose sodium, glycerin, iodopropynyl butylcarbamate, kaolin, petrolatum, phenoxyethanol, polyacrylic acid, polysorbate 80, povidone, propylene glycol, sodium polyacrylate, tartaric acid, titanium dioxide, water,

3-(2-ethylhexyloxy)propane-1,2-diol

Questions

Customer Care Help Line

Toll Free 1-833-933-2323
Mon–Fri 6:00 am–5:00 pm PT